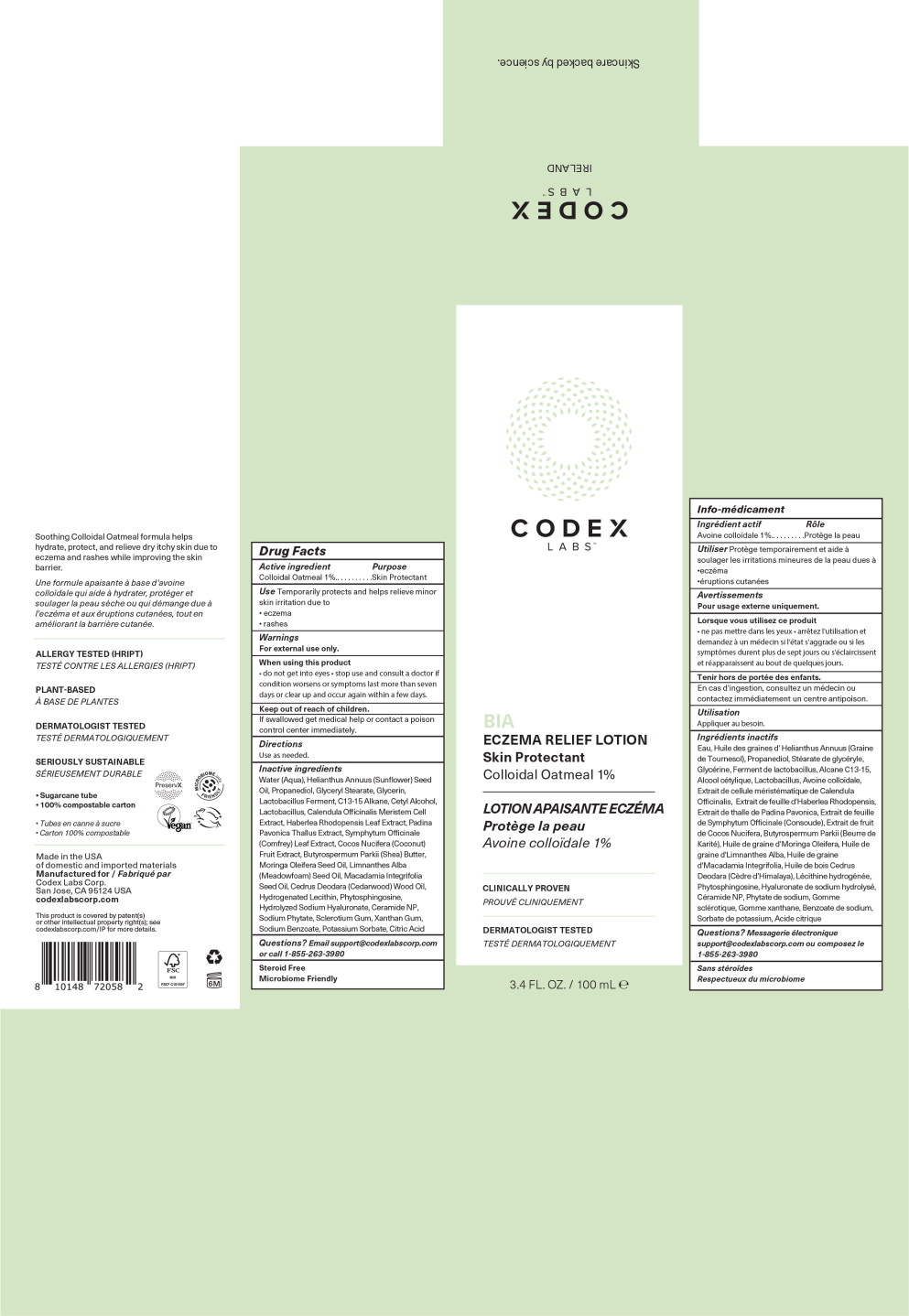 DRUG LABEL: BIA Eczema Relief
NDC: 83196-582 | Form: CREAM
Manufacturer: Codex Labs Corporation
Category: otc | Type: HUMAN OTC DRUG LABEL
Date: 20250127

ACTIVE INGREDIENTS: Oatmeal 10 mg/1 mL
INACTIVE INGREDIENTS: WATER; SUNFLOWER OIL; PROPANEDIOL; GLYCERYL MONOSTEARATE; GLYCERIN; LACTOBACILLUS ACIDOPHILUS; C13-15 ALKANE; CETYL ALCOHOL; CALENDULA OFFICINALIS WHOLE; PADINA PAVONICA; BETASIZOFIRAN; COMFREY LEAF; COCONUT; SODIUM BENZOATE; HABERLEA RHODOPENSIS LEAF; POTASSIUM SORBATE; ANHYDROUS CITRIC ACID; CEDRUS DEODARA WOOD OIL; PHYTATE SODIUM; XANTHAN GUM; HYALURONATE SODIUM; SHEA BUTTER; CERAMIDE NP; MORINGA OLEIFERA SEED OIL; PHYTOSPHINGOSINE; MEADOWFOAM SEED OIL; MACADAMIA OIL; HYDROGENATED SOYBEAN LECITHIN

Drug Facts

Active ingredient

Colloidal Oatmeal 1%

Purpose

Skin Protectant

Use

Temporarily protects and helps relieve minor skin irritation due to

- eczema
- rashes

Warnings

For external use only.

When using this product

- do not get into eyes

- stop use and consult a doctor if condition worsens or symptoms last more than seven days or clear up and occur again within a few days.

Keep out of reach of children.

If swallowed get medical help or contact a poison control center immediately.

Directions

Use as needed.

Inactive ingredients

Water (Aqua), Helianthus Annuus (Sunflower) Seed Oil, Propanediol, Glyceryl Stearate, Glycerin, Lactobacillus Ferment, C13-15 Alkane, Cetyl Alcohol, Lactobacillus, Calendula Officinalis Meristem Cell Extract, Haberlea Rhodopensis Leaf Extract, Padina Pavonica Thallus Extract, Symphytum Officinale (Comfrey) Leaf Extract, Cocos Nucifera (Coconut) Fruit Extract, Butyrospermum Parkii (Shea) Butter, Moringa Oleifera Seed Oil, Limnanthes Alba (Meadowfoam) Seed Oil, Macadamia Integrifolia Seed Oil, Cedrus Deodara (Cedarwood) Wood Oil, Hydrogenated Lecithin, Phytosphingosine, Hydrolyzed Sodium Hyaluronate, Ceramide NP, Sodium Phytate, Sclerotium Gum, Xanthan Gum, Sodium Benzoate, Potassium Sorbate, Citric Acid

Questions?

Email support@codexlabscorp.com or call 1-855-263-3980

Steroid Free

Microbiome Friendly

Principal Display Panel – 100 mL Carton Label

CODEX
LABS™

BIA

ECZEMA RELIEF LOTION

Skin Protectant

Colloidal Oatmeal 1%

3.4 FL. OZ. / 100 mL ℮